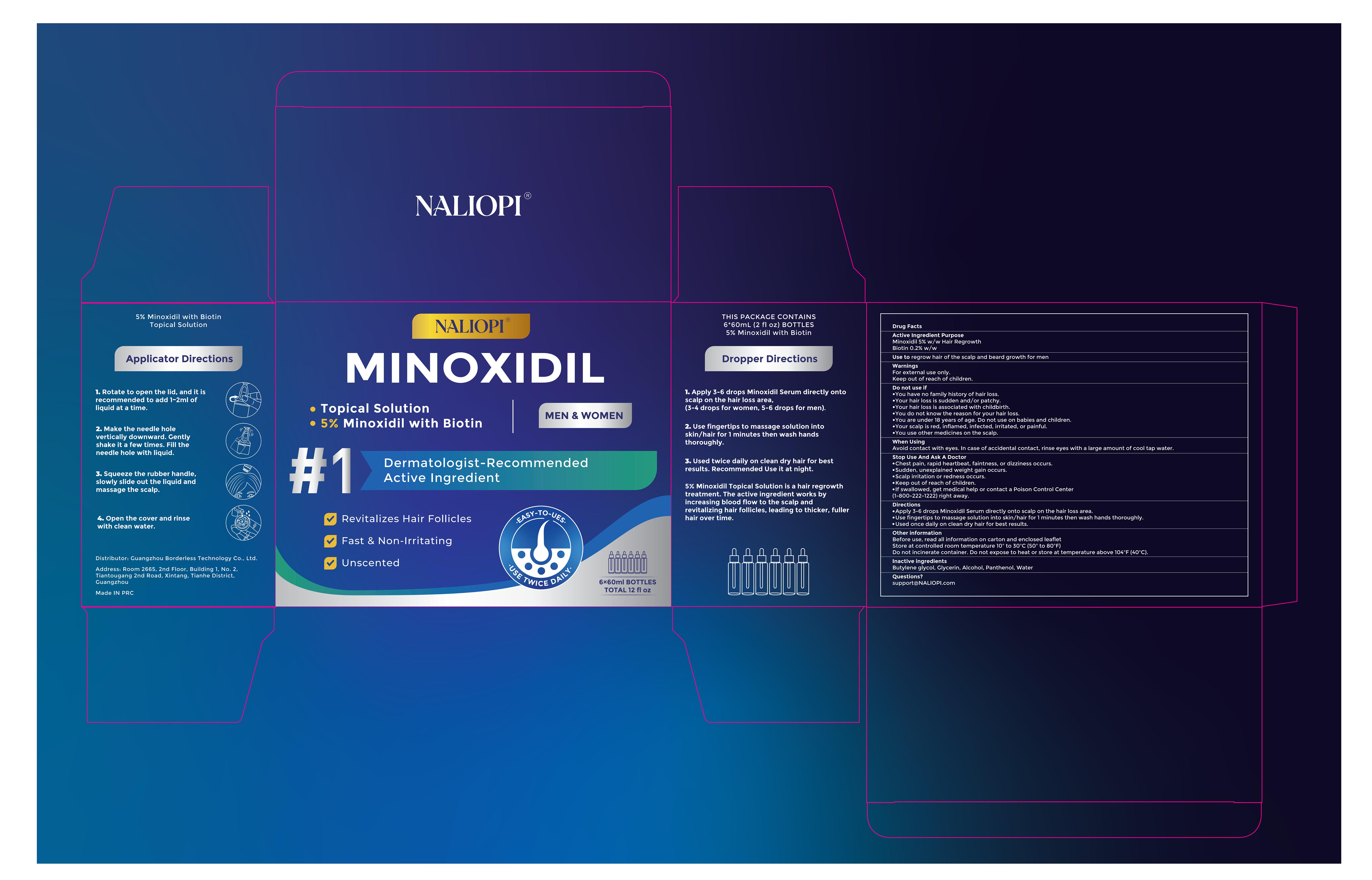 DRUG LABEL: NALIOPI 5% minoxidil with biotin topical solution
NDC: 85304-026 | Form: LIQUID
Manufacturer: Guangzhou Borderless Technology Co., Ltd.
Category: otc | Type: HUMAN OTC DRUG LABEL
Date: 20260224

ACTIVE INGREDIENTS: BIOTIN 0.002 g/1 mL; MINOXIDIL 0.05 g/1 mL
INACTIVE INGREDIENTS: GLYCERIN; WATER; BUTYLENE GLYCOL; ALCOHOL; PANTHENOL

85304-026 NALIOPI 5% minoxidil with biotin topical solution

ACTIVE INGREDIENT

Minoxidil 5%
Biotin 0.2%

PURPOSE

Hair Regrowth

INDICATIONS AND USAGE

Use to regrow hair of the scalp and beard growth for men

WARNINGS

For external use only.
Keep out of reach of children.

DO NOT USE

You have no family history of hair loss.
Your hair loss is sudden and/or patchy.
Your hair loss is associated with childbirth.
You do not know the reason for your hair loss.
You are under 18 years of age. Do not use on babies and children.
Your scalp is red, inflamed, infected, irritated, or painful.
You use other medicines on the scalp.

WHEN USING

Avoid contact with eyes. In case of accidental contact, rinse eyes with a large amount of cool tap water.

STOP USE

Chest pain, rapid heartbeat, faintness, or dizziness occurs.
Sudden, unexplained weight gain occurs.
Scalp irritation or redness occurs.
Keep out of reach of children.

lf swallowed, get medical help or contact a Poison Control Center(1-800-222-1222)right away.

Keep out of reach of children.

DOSAGE AND ADMINISTRATION

Apply 3-6 drops Minoxidil Serum directly onto scalp on the hair loss area.

Use fingertips to massage solution into skin/hair for 1 minutes then wash hands thoroughly

Used once daily on clean dry hair for best results.

INACTIVE INGREDIENT

Butylene glycol, Glycerin, Alcohol, Panthenol, Water